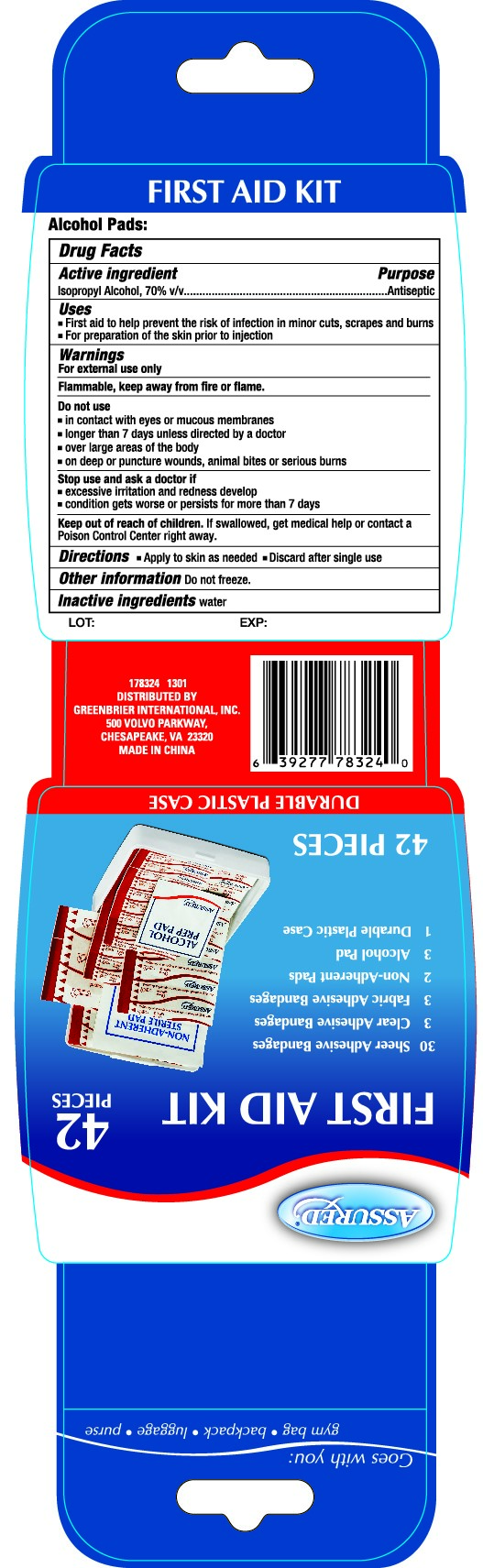 DRUG LABEL: Assured
NDC: 44019-008 | Form: PATCH
Manufacturer: Yinjing Medical Technology (Shanghai) Co., Ltd.
Category: otc | Type: HUMAN OTC DRUG LABEL
Date: 20160813

ACTIVE INGREDIENTS: ISOPROPYL ALCOHOL .70 mL/1 mL
INACTIVE INGREDIENTS: WATER

Drug Facts

Inactive Ingredients: Water

Active Ingredient

Isopropyl Alcohol 70% v/v

Purpose

Antiseptic

Keep out of reach of children If swallowed, get medical help or contact a Poison Control Center right away.

Uses

First aid to help prevent the risk of infection in minor cuts, scrapes and burns

For preparation of the skin prior to injection

Warnings

For external use only

Flammable. Keep away from fire or flame

Directions

Apply to skin as needed

Discard after single use

Do not use

-in contact with eyes or with mucous membranes

-more than 7 days unless directed by a doctor

-over large areas of the body

-on deep or puncture wounds, animal bites or serious burns

Stop use and ask a doctor if

-excessive irritation and redness develop

-condition gets worse or persists for more than 7 days